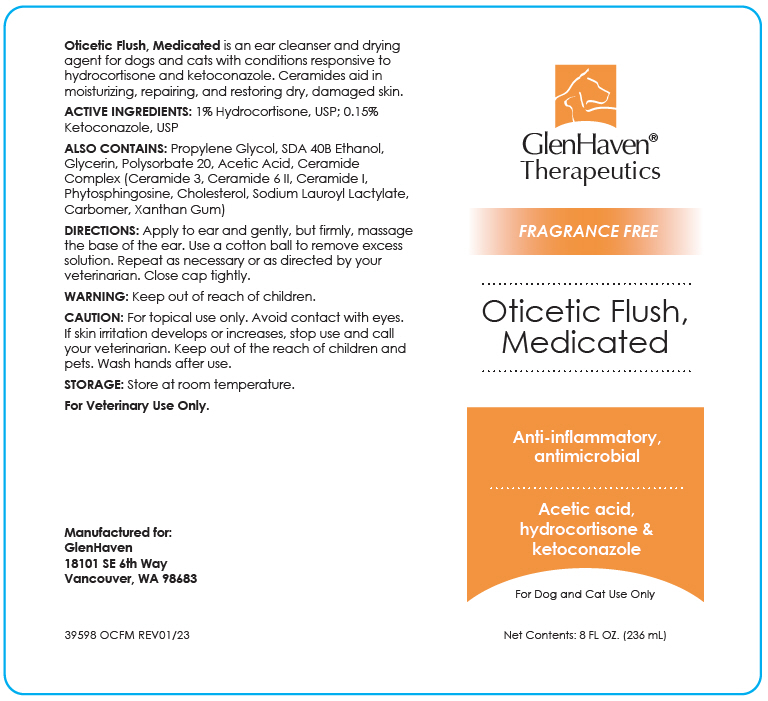 DRUG LABEL: Oticetic Flush, Medicated
NDC: 70782-143 | Form: SOLUTION
Manufacturer: GlenHaven LLC
Category: animal | Type: OTC ANIMAL DRUG LABEL
Date: 20230608

ACTIVE INGREDIENTS: Hydrocortisone 10 mg/1 mL; Ketoconazole 1.5 mg/1 mL

Oticetic Flush, Medicated

VETERINARY INDICATIONS

Oticetic Flush, Medicated is an ear cleanser and drying agent for dogs and cats with conditions responsive to hydrocortisone and ketoconazole. Ceramides aid in moisturizing, repairing, and restoring dry, damaged skin.

ACTIVE INGREDIENT

ACTIVE INGREDIENTS: 1% Hydrocortisone, USP; 0.15% Ketoconazole, USP

DESCRIPTION

ALSO CONTAINS: Propylene Glycol, SDA 40B Ethanol, Glycerin, Polysorbate 20, Acetic Acid, Ceramide Complex (Ceramide 3, Ceramide 6 II, Ceramide I, Phytosphingosine, Cholesterol, Sodium Lauroyl Lactylate, Carbomer, Xanthan Gum)

DOSAGE AND ADMINISTRATION

DIRECTIONS: Apply to ear and gently, but firmly, massage the base of the ear. Use a cotton ball to remove excess solution. Repeat as necessary or as directed by your veterinarian. Close cap tightly.

WARNINGS

WARNING: Keep out of reach of children.

SAFE HANDLING WARNING

CAUTION: For topical use only. Avoid contact with eyes. If skin irritation develops or increases, stop use and call your veterinarian. Keep out of the reach of children and pets. Wash hands after use.

STORAGE: Store at room temperature.

For Veterinary Use Only.

Manufactured for:
GlenHaven
18101 SE 6th Way
Vancouver, WA 98683

39598 OCFM REV01/23

PRINCIPAL DISPLAY PANEL - 236 mL Bottle Label

GlenHaven®
Therapeutics

FRAGRANCE FREE

Oticetic Flush,
Medicated

Anti-inflammatory,
antimicrobial

Acetic acid,
hydrocortisone &
ketoconazole

For Dog and Cat Use Only

Net Contents: 8 FL OZ. (236 mL)